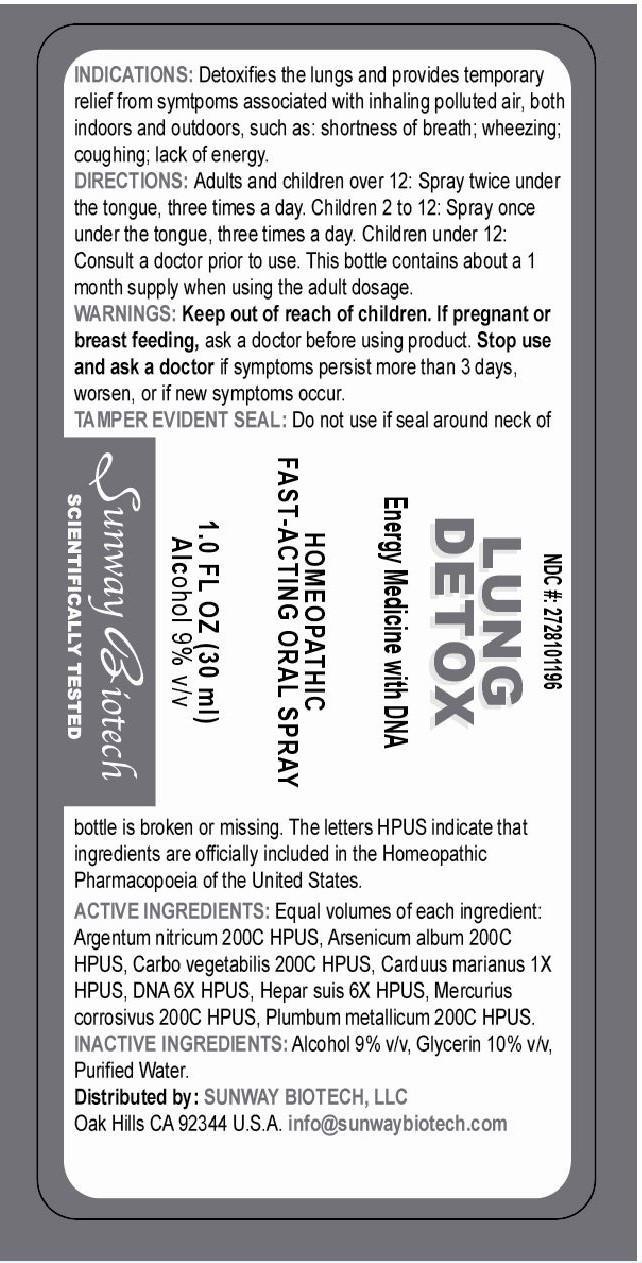 DRUG LABEL: Lung Detox
NDC: 55138-011 | Form: SPRAY
Manufacturer: Integra Health International S.A. de C.V.
Category: homeopathic | Type: HUMAN OTC DRUG LABEL
Date: 20140808

ACTIVE INGREDIENTS: SILVER NITRATE 200 [hp_C]/1 mg; ARSENIC TRIOXIDE 200 [hp_C]/1 mg; ACTIVATED CHARCOAL 200 [hp_C]/1 mg; SILYBUM MARIANUM SEED 0.5 [hp_C]/1 mg; HERRING SPERM DNA 3 [hp_C]/1 mg; PORK LIVER 3 [hp_C]/1 mg; MERCURIC CHLORIDE 200 [hp_C]/1 mg; LEAD 200 [hp_C]/1 mg
INACTIVE INGREDIENTS: ALCOHOL; GLYCERIN; WATER

Active Ingredients: Equal volumes of each ingredient:

argentum nitricum 200C HPUS, arsenicum album 200C HPUS, carbo vegetabilis 200C HPUS, carduus marianus 1X HPUS, DNA 6X HPUS, hepar suis 6X HPUS, mercurius corrosivus 200C HPUS, plumbum metallicum 200C HPUS.

PURPOSE

Lung Detox

Energy Medicine with DNA

Homeopathic Fast-Acting Oral Spray

1.0 Fl Oz (30 ml)

Alcohol 9% v/v

Sunway Biotech

Scientifically Tested

Keep out of reach of children.

INDICATIONS AND USAGE

Indications: Detoxifies the lungs and provides temporary relief from symtpoms associated with inhaling polluted air, both indoors and outdoors, such as: shortness of breath; wheezing; coughing; lack of energy.

WARNINGS

Warnings: If pregnant or breast feeding, ask a doctor before using product. Stop use and ask a doctor if symptoms persist more than 3 days, worsen, or if new symptoms occur.

Tamper Evident Seal: do not use if seal around neck of bottle is broken or missing. The letters HPUS indicate that ingredients are officially included in the Homoepathic Pharmacopoeia of the United States.

DOSAGE AND ADMINISTRATION

Directions: Adults and children over 12: spray twice under the tongue, three times a day. Children 2 to 12: spray once under the tongue, three times a day. Children under 12: consult a doctor prior to suse. This bottle contains about a 1 month supply when using the adult dosage.

INACTIVE INGREDIENT

Inactive Ingredients: alcohol 9% v/v, glycerin 10% v/v, purified water.